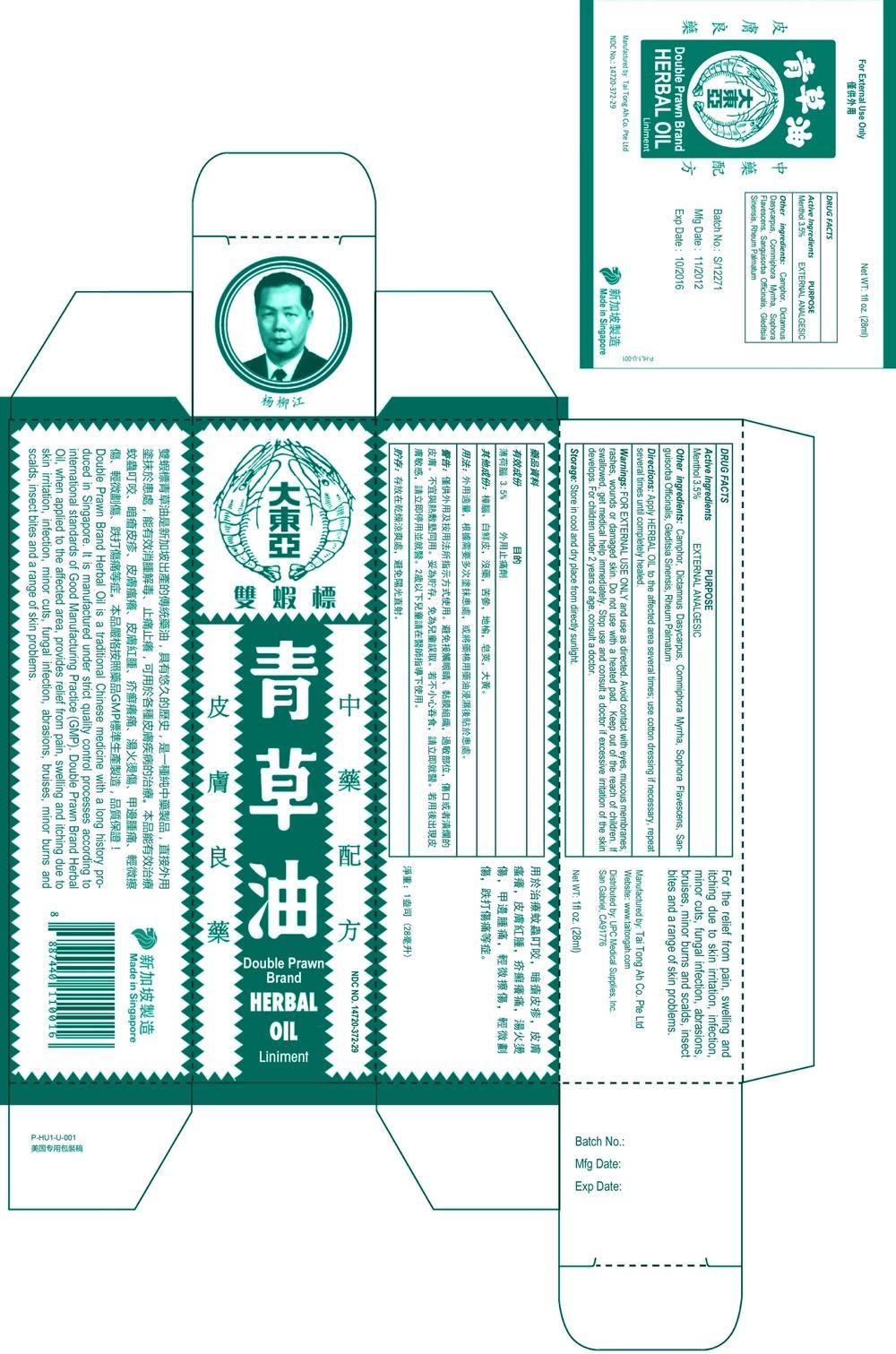 DRUG LABEL: Double Prawn Brand Herbal Oil
NDC: 14720-372 | Form: OIL
Manufacturer: Tai Tong Ah Co Pte Ltd
Category: otc | Type: HUMAN OTC DRUG LABEL
Date: 20131111

ACTIVE INGREDIENTS: MENTHOL 3.5 g/100 mL
INACTIVE INGREDIENTS: CAMPHOR (SYNTHETIC); DICTAMNUS DASYCARPUS WHOLE; COMMIPHORA MYRRHA WHOLE; SOPHORA FLAVESCENS WHOLE; SANGUISORBA OFFICINALIS WHOLE; GLEDITSIA SINENSIS WHOLE; RHEUM PALMATUM WHOLE

Double Prawn Brand Herbal Oil

ACTIVE INGREDIENTS

Menthol 3.5%

PURPOSE

Menthol External Analgesic

USE

For the relief from pain, swelling and itching due to skin irritation, skin infection, minor cuts, fungal infection, abrasions, bruises, minor burns and scalds, insect bites and a range of skin problems.

WARNING

For external use only and use as directed. Avoid contact with eyes, mucous membrances or rashes, wounds or damage skin. Do not use with a heated pad.

WARNING

Keep out of reach of children. If swallowed, get medical help immediately.

WARNING

Stop use and consult a doctor if excessive irritaion of the skin develops. For children under 2 years of age, consult a doctor.

DIRECTIONS

Apply Herbal Oil to the affective area several times; use cotton dressing if necessary, repeat several times until completely healed.

DIRECTIONS

Apply Herbal Oil several times daily.

STORAGE

Store at cool and dry place from direct sunlight.

INACTIVE INGREDIENT

Camphor, dictampus dasycarpus, commiphora myrrha, sophora flavescens, sanguisorba officinalis, gleditsia sinensis, rheum palamatum